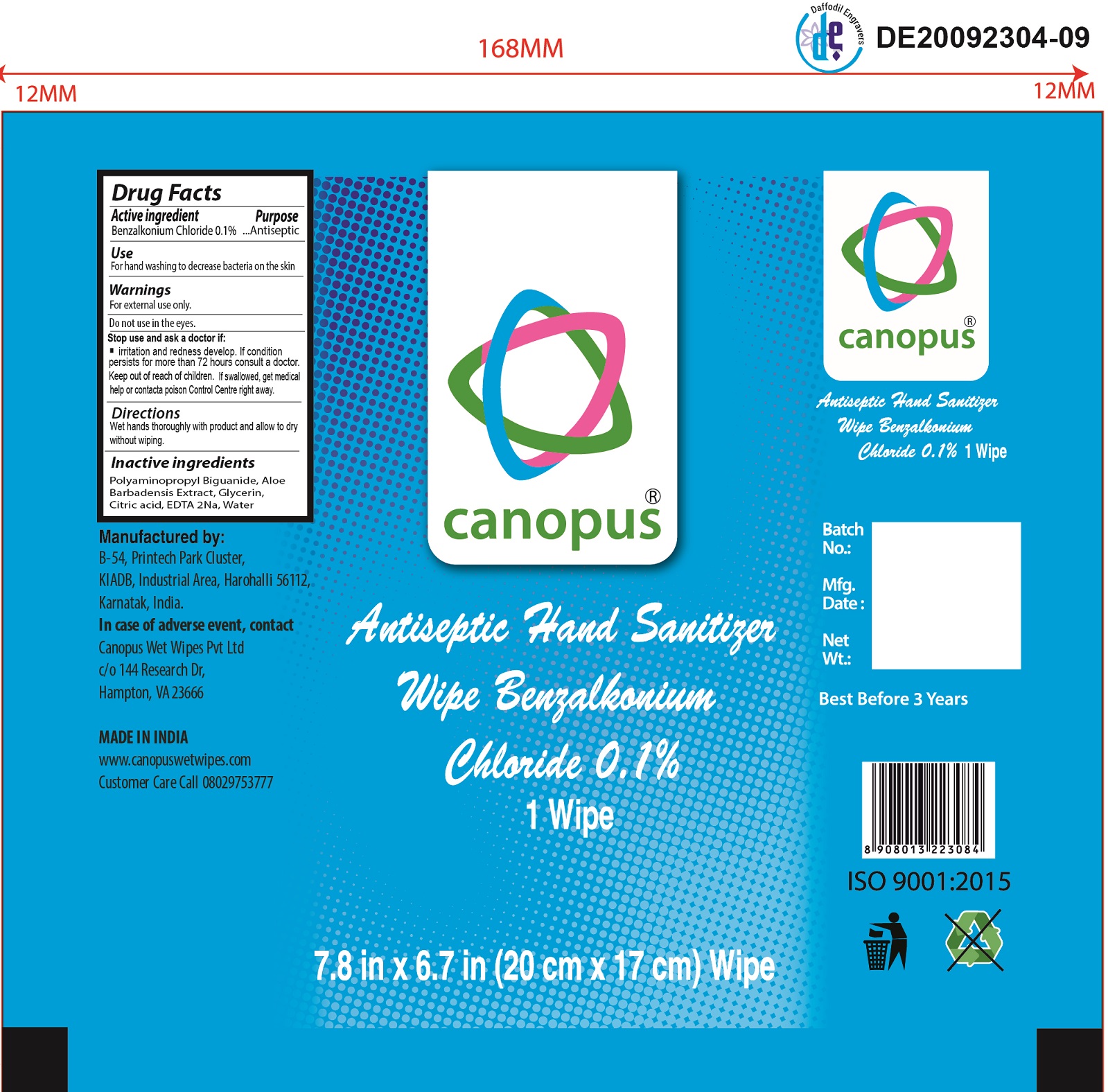 DRUG LABEL: Antiseptic Hand Sanitizer Wipe Benzalkonium Chloride
NDC: 81063-000 | Form: CLOTH
Manufacturer: CANOPUS WET WIPES PRIVATE LIMITED
Category: otc | Type: HUMAN OTC DRUG LABEL
Date: 20240116

ACTIVE INGREDIENTS: BENZALKONIUM CHLORIDE 1 mg/1 mL
INACTIVE INGREDIENTS: ALOE VERA LEAF; GLYCERIN; POLYAMINOPROPYL BIGUANIDE; CITRIC ACID MONOHYDRATE; EDETIC ACID; WATER

Antiseptic Hand Sanitizer Wipe - Benzalkonium Chloride

Active ingredient

Benzalkonium Chloride 0.1%

Purpose

Antiseptic

Use

For hand washing to decrease bacteria on ths skin

Warnings

For external use only.

Do not use

in the eyes.

Stop use and ask a doctor if:

irritation and redness develop. If condition persists for more than 72 hours consult a doctor.

Keep out of reach of children.

If swallowed, get medical help or contact poison Control Centre right away.

Directions

Wet hands thoroughly with product and allow to dry without wiping.

Inactive ingredients

Polyaminopropyl Biguanide, Aloe Barbadensis Extract, Glycerin, Citric acid, EDTA 2Na, Water